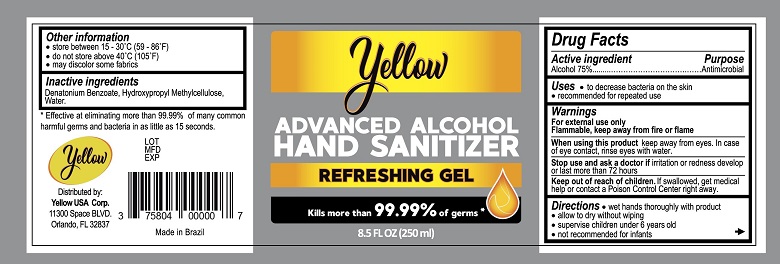 DRUG LABEL: Yellow Hand Sanitizer
NDC: 75804-001 | Form: LIQUID
Manufacturer: Yellow USA Toy Corp
Category: otc | Type: HUMAN OTC DRUG LABEL
Date: 20200708

ACTIVE INGREDIENTS: ALCOHOL 75 mL/100 mL
INACTIVE INGREDIENTS: DENATONIUM BENZOATE; WATER; HYPROMELLOSE, UNSPECIFIED

Yellow Hand Sanitizer

Drug Facts

Active ingredient

Alcohol 75%

Purpose
Antimicrobial

Uses

- to decrease bacteria on the skin
- recommended for repeated use

Warnings
For external use only
Flammable. Keep away from heat or flame

When using this product keep away from eyes. In case of eye contact, rinse eyes with water.

Stop use and ask a doctor if irritation or redness develop or last more than 72 hours.

Keep out of reach of children. If swallowed, get medical help or contact a Poison Control Center immediately.

Directions

- wet hands thoroughly with product
- allow to dry without wiping
- supervise children under 6 years old
- not recommended for infants

Other information

- store between 15-30°F(59-86°C)
- do not store above 40°C (105°F)
- may discolor some fabrics

Inactive ingredients

Denatonium Benzoate, Hydroxypropyl Methylcellulose, Water

Distributed by:

Yellow USA Corp.

11300 Space BLVD, Orlando, FL 32837

Made in Brazil

PACKAGE LABEL

Yellow

ADVANCED ALCOHOL

HAND SANITIZER

REFRESHING GEL

8.5 FL OZ (250 ml)